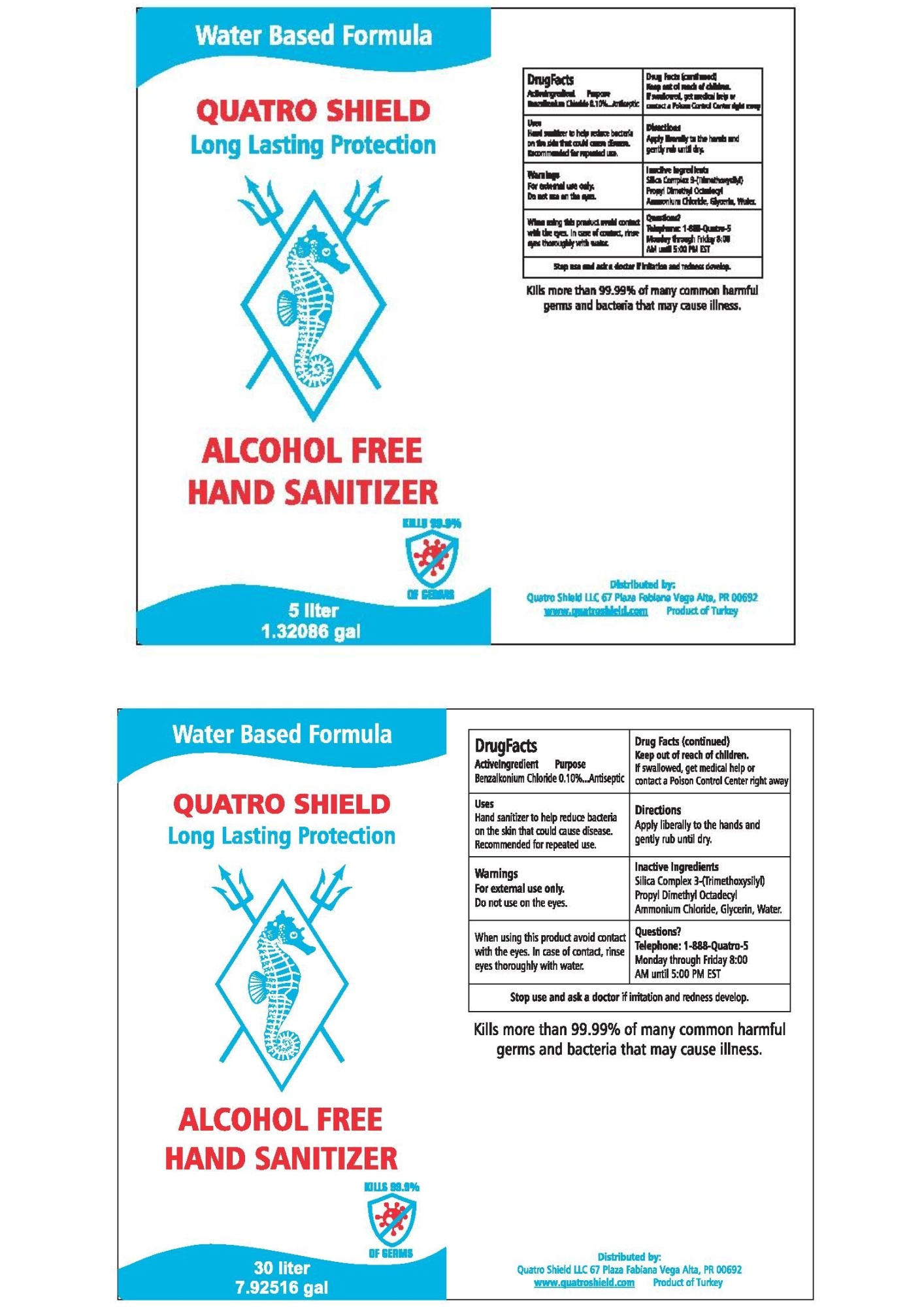 DRUG LABEL: Quatro Shield Hand Sanitizer
NDC: 78873-610 | Form: LIQUID
Manufacturer: QUATRO SHIELD LLC
Category: otc | Type: HUMAN OTC DRUG LABEL
Date: 20200626

ACTIVE INGREDIENTS: BENZALKONIUM CHLORIDE 0.1 kg/100 L
INACTIVE INGREDIENTS: GLYCERIN; DIMETHYLOCTADECYL(3-(TRIMETHOXYSILYL)PROPYL)AMMONIUM CHLORIDE; WATER

Liquid

Active Ingredient(s)

BENZALKONIUM CHLORIDE 0.10%

Purpose

Antiseptic

Use

Hand Sanitizer to help reduce bacteria on the skin that potentially could cause disease. Recommended for repeated use.

Warnings

For external use only. Do not use on the eyes.

When using this product avoid contact with the eyes. In case of contact with eyes, rinse eyes thoroughly with water.

Keep out of reach of children. If swallowed, get medical help or contact a Poison Control Center right away.

Directions

APPLY LIBERALLY TO THE HANDS AND GENTLY RUB UNTIL DRY.

Inactive ingredients

SILICA COMPLEX 3-(TRIMETHOXYSILYL) PROPYL DIMETHYL OCTADECYL AMMONIUM CHLORIDE, GLYCERIN, WATER

Stop use and ask a doctor if irritation and redness develop

QUESTIONS

1-888-QUATRO-5

MONDAY THROUGH FRIDAY 8:00 AM UNTIL 5:00 PM EST

Package Label - Principal Display Panel

WATER BASED FORMULA

QUATRO SHIELD

LONG-LASTING PROTECTION

ALCOHOL-FREE

HAND SANITIZER

KILLS 99.9% OF GERMS

Kills more than 99.99% of many common harmful germs and bacteria that may cause ilnness.

Distributed by:

Quatro Shield LLC

67 Plaza Fabiana

Vega Alta, PR 00692

www.Quatroshield.com

Product of Turkey